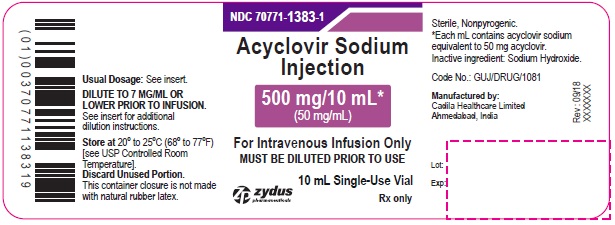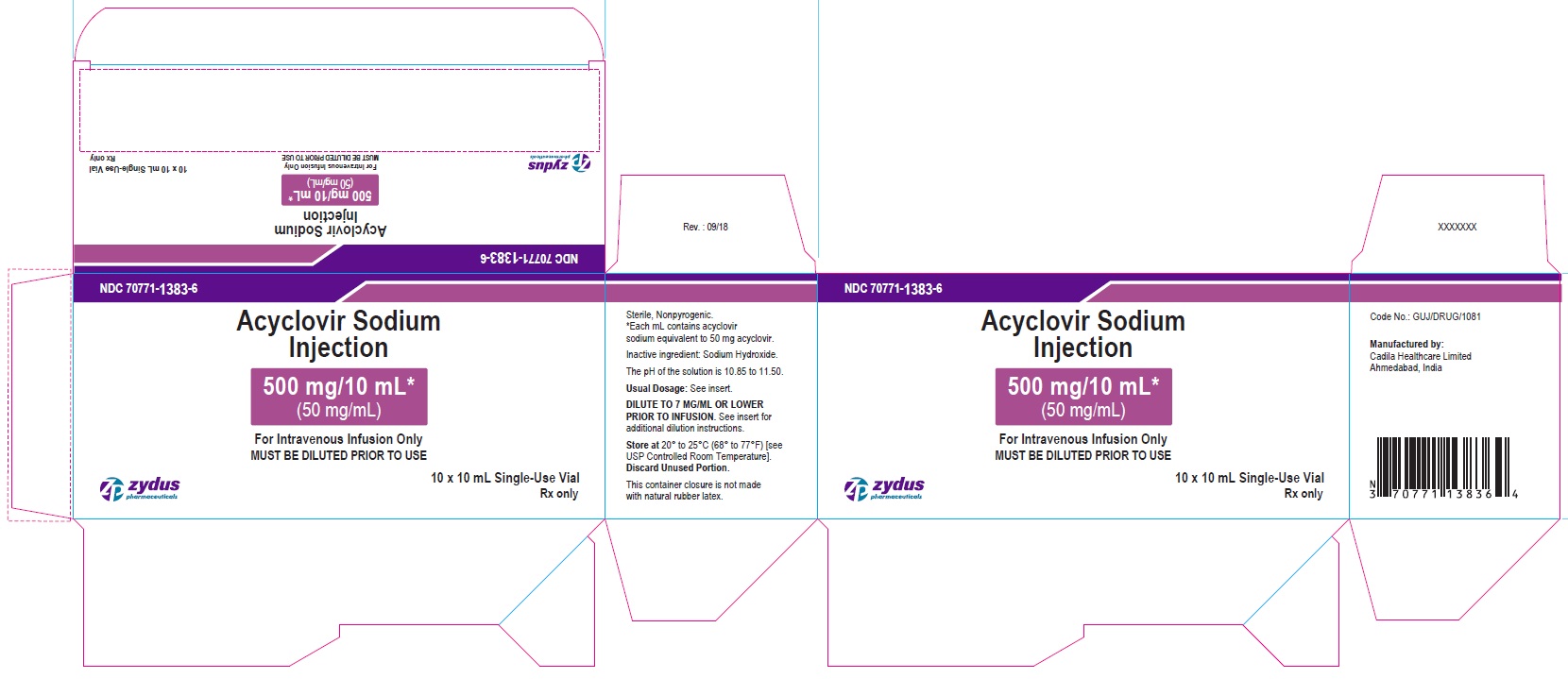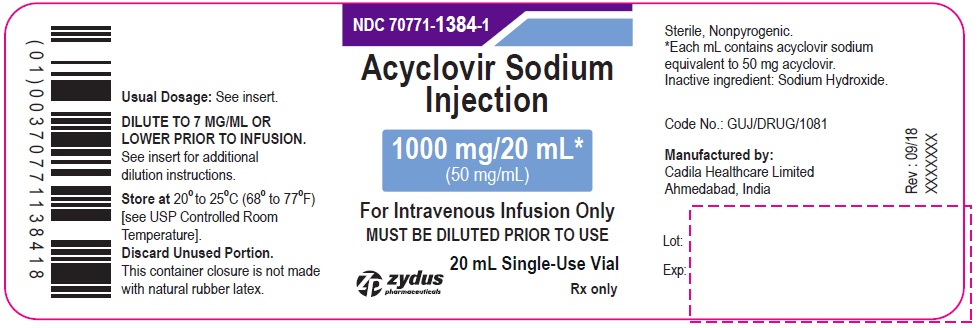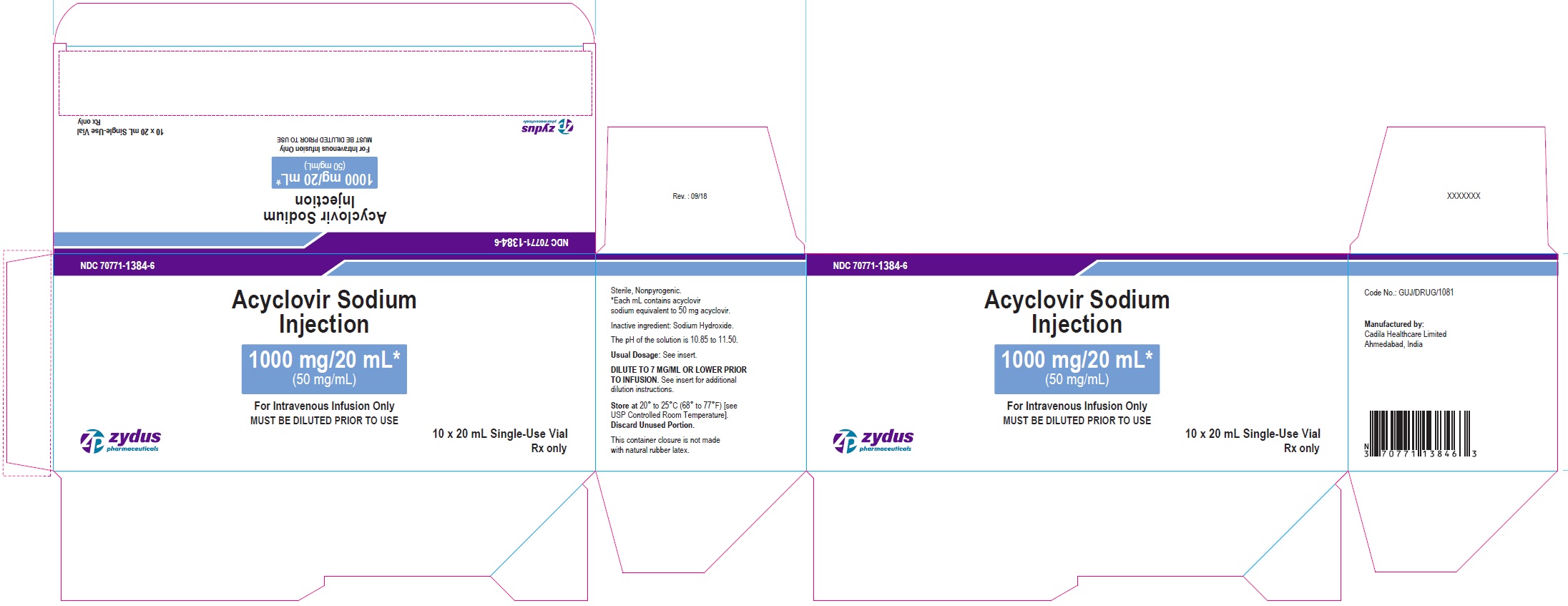 DRUG LABEL: acyclovir
NDC: 70771-1383 | Form: INJECTION, SOLUTION
Manufacturer: Zydus Lifesciences Limited
Category: prescription | Type: HUMAN PRESCRIPTION DRUG LABEL
Date: 20221017

ACTIVE INGREDIENTS: ACYCLOVIR SODIUM 50 mg/1 mL
INACTIVE INGREDIENTS: SODIUM HYDROXIDE; WATER

Acyclovir Sodium Injection

PACKAGE LABEL.PRINCIPAL DISPLAY PANEL

PACKAGE LABEL - PRINCIPAL DISPLAY - 10 mL Single-Use Container Label

NDC 70771-1383-1

Acyclovir Sodium Injection

500 mg/10 mL*

(50 mg/mL)

For Intravenous Infusion Only

MUST BE DILUTED PRIOR TO USE

10 mL Single-Use Vial

Rx only

zydus pharmaceuticals

PACKAGE LABEL - PRINCIPAL DISPLAY - 10 mL Single-Use Carton Label

NDC 70771-1383-6

Acyclovir Sodium Injection

500 mg/10 mL*

(50 mg/mL)

For Intravenous Infusion Only

MUST BE DILUTED PRIOR TO USE

10 x 10 mL Single-Use Vial

Rx only

zydus pharmaceuticals

PACKAGE LABEL - PRINCIPAL DISPLAY - 20 mL Single-Use Container Label

NDC 70771-1384-1

Acyclovir Sodium Injection

1000 mg/20 mL*

(50 mg/mL)

For Intravenous Infusion Only

MUST BE DILUTED PRIOR TO USE

20 mL Single-Use Vial

Rx only

zydus pharmaceuticals

PACKAGE LABEL - PRINCIPAL DISPLAY - 20 mL Single-Use Carton Label

NDC 70771-1384-6

Acyclovir Sodium Injection

1000 mg/20 mL*

(50 mg/mL)

For Intravenous Infusion Only

MUST BE DILUTED PRIOR TO USE

10 x 20 mL Single-Use Vial

Rx only

zydus pharmaceuticals